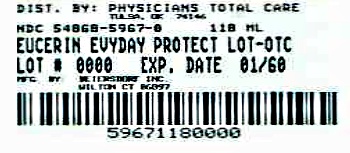 DRUG LABEL: Eucerin
NDC: 54868-5967 | Form: LOTION
Manufacturer: Physicians Total Care, Inc.
Category: otc | Type: HUMAN OTC DRUG LABEL
Date: 20120522

ACTIVE INGREDIENTS: Octinoxate 7.5 mL/100 mL; Zinc Oxide 4.85 mL/100 mL; Octisalate 4.5 mL/100 mL; Ensulizole 2 mL/100 mL; Titanium Dioxide 2.38 mL/100 mL
INACTIVE INGREDIENTS: WATER; GLYCERIN; C12-15 ALKYL BENZOATE; DIMETHICONE; CYCLOMETHICONE; CETYL ALCOHOL; CETOSTEARYL ALCOHOL; POLYOXYL 20 CETOSTEARYL ETHER; GLYCERYL MONOSTEARATE; SODIUM LACTATE; LACTIC ACID; COCO-GLYCERIDES; POLYOXYL 40 CASTOR OIL; SODIUM CETOSTEARYL SULFATE; XANTHAN GUM; EDETATE TRISODIUM; SODIUM HYDROXIDE; ALUMINUM OXIDE; PHENOXYETHANOL; DMDM HYDANTOIN

Eucerin Everyday Protection Face

DOSAGE AND ADMINISTRATION

Enter section text here

INACTIVE INGREDIENT

Water, Glycerin, C12-15
Alkyl Benzoate, Dimethicone, Cyclomethicone,
Cetyl Alcohol, Cetearyl Alcohol, Ceteareth-
20, Glyceryl Stearate SE, Sodium Lactate,
Lactic Acid, Hydrogenated Coco-
Glycerides, VP/Hexadecene Copolymer,
PEG-40 Castor Oil, Sodium Cetearyl Sulfate,
Xanthan Gum, Trisodium EDTA, Sodium
Hydroxide, Alumina, Simethicone,
Phenoxyethanol, DMDM Hydantoin

INDICATIONS AND USAGE

Use a gentle cleanser such as Eucerin Gentle Hydrating Cleanser.
After cleansing apply to face and neck every morning

ACTIVE INGREDIENT

Octinoxate, Zinc Oxide,Octisalate, Ensulizole, Titanium Dioxide

Stop use and consult a doctor if irritation develops

Keep out of reach of children

Questions Comments 1-800-227-4703

WARNINGS

For external use only. Keep out of eyes

PACKAGE LABEL

NDC 54868-5967-0

Eucerin

Dermatologist Recommended

Sensitive Skin

Everyday Protection Face Lotion

UVA + UVB SPF 30 Protection

Non-Comedogenic · Fragrance-Free

DERMATOLOGICAL SKINCARE

4 FL.OZ. 118mL